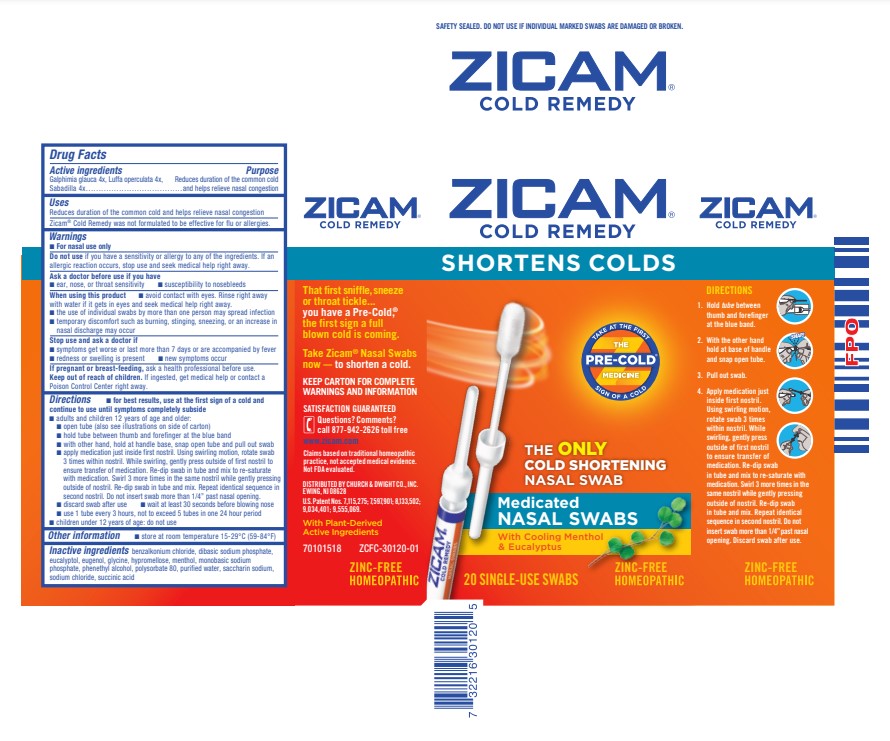 DRUG LABEL: Zicam Cold Remedy
NDC: 10237-472 | Form: GEL
Manufacturer: Church & Dwight Co., Inc.
Category: homeopathic | Type: HUMAN OTC DRUG LABEL
Date: 20241121

ACTIVE INGREDIENTS: GALPHIMIA GLAUCA FLOWERING TOP 4 [hp_X]/1.2 mL; LUFFA OPERCULATA FRUIT 4 [hp_X]/1.2 mL; SCHOENOCAULON OFFICINALE SEED 4 [hp_X]/1.2 mL
INACTIVE INGREDIENTS: BENZALKONIUM CHLORIDE; SODIUM PHOSPHATE, DIBASIC, UNSPECIFIED FORM; EUCALYPTOL; EUGENOL; GLYCINE; HYPROMELLOSE, UNSPECIFIED; MENTHOL, UNSPECIFIED FORM; SODIUM PHOSPHATE, MONOBASIC, UNSPECIFIED FORM; PHENYLETHYL ALCOHOL; POLYSORBATE 80; WATER; SACCHARIN SODIUM; SODIUM CHLORIDE; SUCCINIC ACID

Zicam® Cold Remedy Medicated Nasal Swabs

Drug Facts

Active ingredients

Galphimia glauca 4x, Luffa operculata 4x, Sabadilla 4x

Purpose

Reduces duration and severity of the common cold and helps relieve nasal congestion

Uses

Reduces duration of the common cold and helps relieve nasal congestion

Zicam® Cold Remedy was formulated to shorten the duration of the common cold and may not be effective for flu or allergies.

Warnings

- For nasal use only

Do not use if you have a sensitivity or allergy to any of the ingredients. If an allergic reaction occurs, stop use and seek medical help right away.

Ask a doctor before use if you have

- ear, nose, or throat sensitivity
- susceptibility to nosebleeds

When using this product

- avoid contact with eyes. Rinse right away with water if it gets in eyes and seek medical help right away.
- the use of individual swabs by more than one person may spread infection
- temporary discomfort such as burning, stinging, sneezing, or an increase in nasal discharge may occur

Stop use and ask a doctor if

- symptoms get worse or last more than 7 days or are accompanied by fever
- redness or swelling is present
- new symptoms occur

PREGNANCY OR BREAST FEEDING

If pregnant or breast-feeding, ask a health professional before use.

Keep out of reach of children. If swallowed, get medical help or contact a Poison Control Center right away.

Directions

- for best results, use at the first sign of a cold and continue to use until symptoms completely subside
- adults and children 12 years of age and older:
  - open tube (also see illustration on side of carton)
  - hold tube between thumb and forefinger at the blue band
  - with other hand, hold at handle base, snap open tube and pull out swab
  - apply medication just inside first nostril. Using swirling motion, rotate swab 3 times within nostril. While swirling, gently press outside of first nostril to ensure transfer of medication. Re-dip swab in tube and mix to re-saturate with medication. Swirl 3 more times in the same nostril while gently pressing outside of nostril. Re-dip swab in tube and mix. Repeat identical sequence in second nostril. Do not insert swab more than 1/4" past nasal opening.
  - discard swab after use
  - wait at least 30 seconds before blowing nose
  - use 1 tube every 3 hours, not to exceed 5 tubes in one 24 hour period
- children under 12 years of age: do not use

Other information

- store at room temperature 15-29°C (59-84°F)

Inactive ingredients

benzalkonium chloride, dibasic sodium phosphate, eucalyptol, eugenol, glycine, hypromellose, menthol, monobasic sodium phosphate, phenethyl alcohol, polysorbate 80, purified water, saccharin sodium, sodium chloride, succinic acid

Questions? Comments? Side Effects?

call 877-942-2626 toll free

PRINCIPAL DISPLAY PANEL - 20 Swab Tube Carton

ZICAM®

COLD REMEDY

SHORTENS COLDS

TAKE AT THE FIRST
THE
PRE-COLD®
MEDICINE
SIGN OF A COLD

THE
ONLY
COLD SHORTENING
NASAL SWAB

Medicated

NASAL SWABS

With Cooling Menthol
& Eucalyptus

20 SINGLE-USE SWABS

ZINC-FREE
HOMEOPATHIC